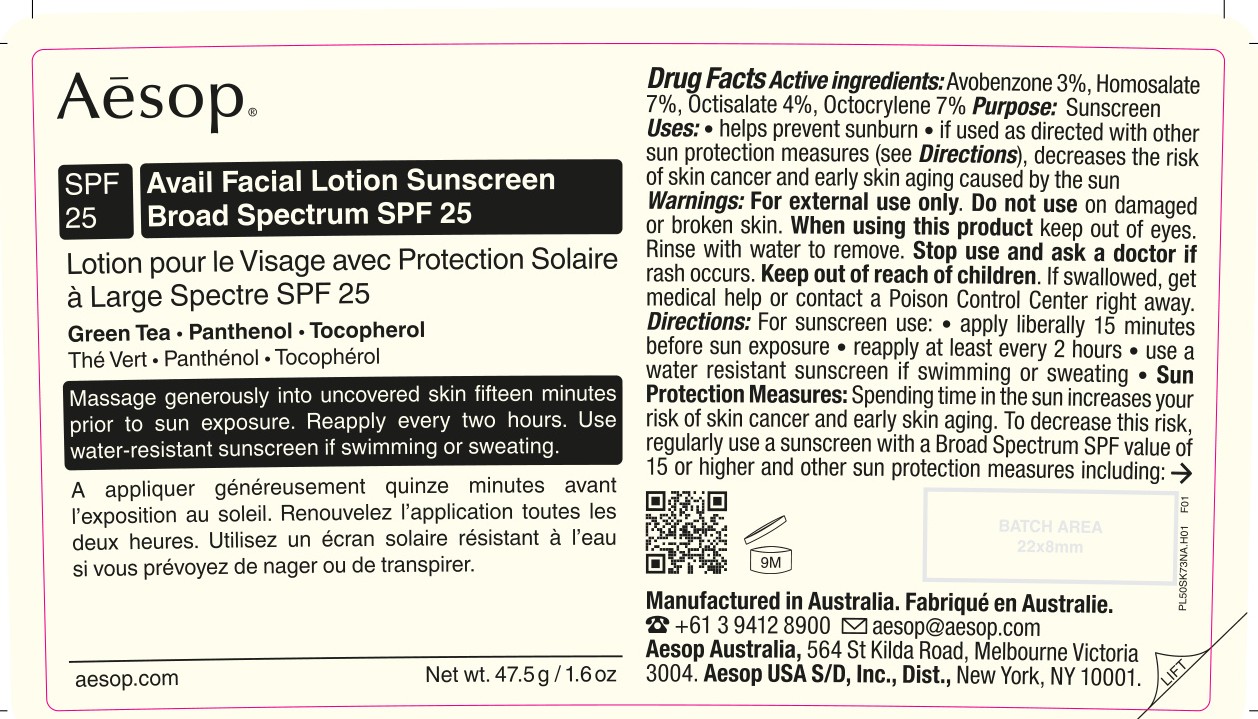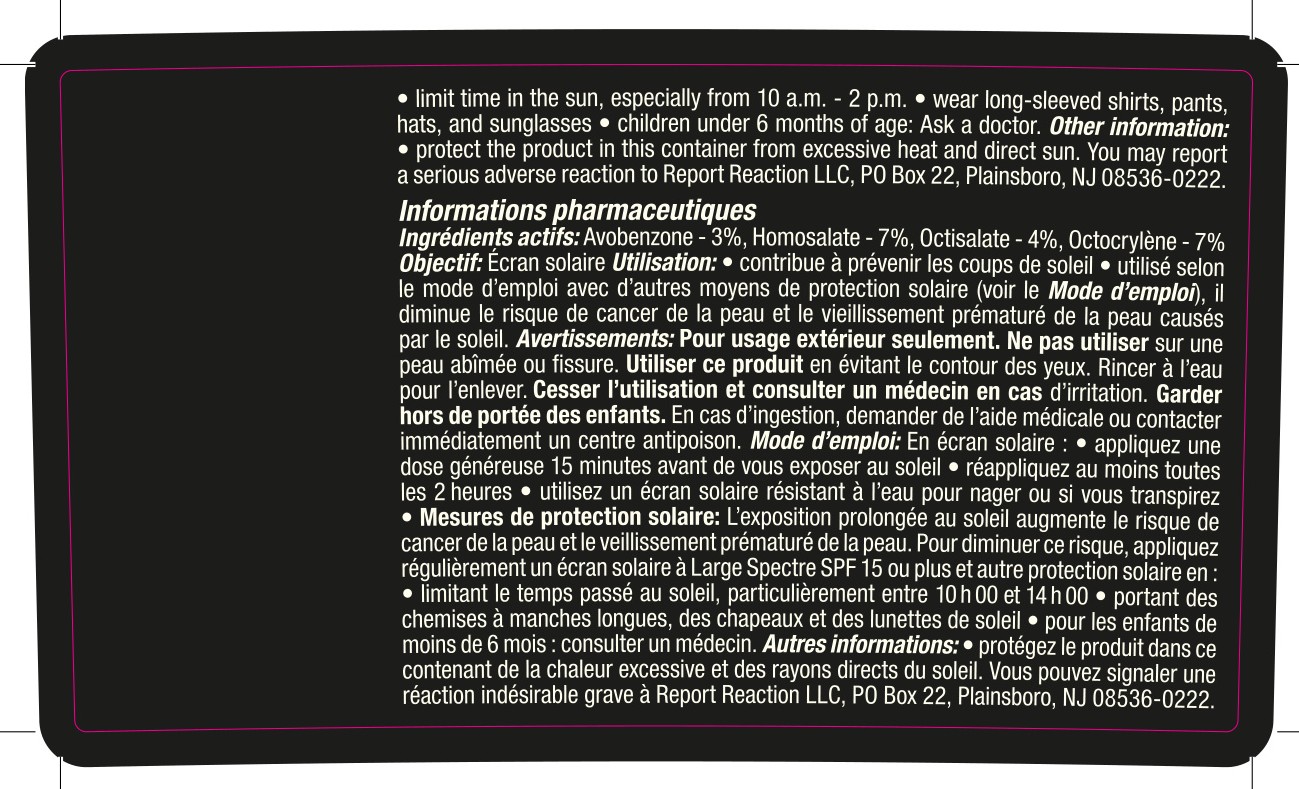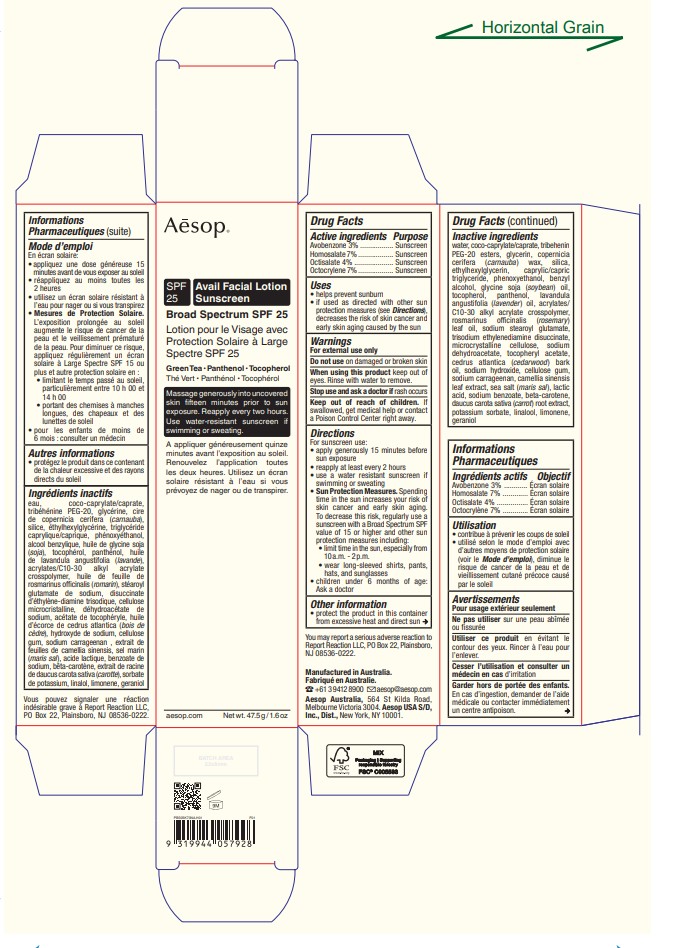 DRUG LABEL: AESOP Avail Facial Sunscreen Broad Spectrum SPF 25
NDC: 76293-928 | Form: LOTION
Manufacturer: Emeis Cosmetics Pty Ltd
Category: otc | Type: HUMAN OTC DRUG LABEL
Date: 20251017

ACTIVE INGREDIENTS: AVOBENZONE 30.0 mg/1 g; HOMOSALATE 70.0 mg/1 g; OCTISALATE 40.0 mg/1 g; OCTOCRYLENE 70.0 mg/1 g
INACTIVE INGREDIENTS: WATER; COCO-CAPRYLATE/CAPRATE; TRIBEHENIN PEG-20 ESTERS; GLYCERIN; COPERNICIA CERIFERA (CARNAUBA) WAX; SILICA; ETHYLHEXYLGLYCERIN; CAPRYLIC/CAPRIC TRIGLYCERIDE; PHENOXYETHANOL; BENZYL ALCOHOL; SOYBEAN OIL; TOCOPHEROL; PANTHENOL; LAVANDULA ANGUSTIFOLIA (LAVENDER) OIL; ACRYLATES/C10-30 ALKYL ACRYLATE CROSSPOLYMER (60000 MPA.S); ROSMARINUS OFFICINALIS (ROSEMARY) LEAF OIL; SODIUM STEAROYL GLUTAMATE; TRISODIUM ETHYLENEDIAMINE DISUCCINATE; MICROCRYSTALLINE CELLULOSE; SODIUM DEHYDROACETATE; .ALPHA.-TOCOPHEROL ACETATE, D-; CEDRUS ATLANTICA BARK OIL; SODIUM HYDROXIDE; CELLULOSE GUM; SODIUM CARRAGEENAN; GREEN TEA LEAF; SEA SALT; LACTIC ACID, DL-; SODIUM BENZOATE; BETA-CAROTENE; CARROT; POTASSIUM SORBATE; LINALOOL; LIMONENE, (+/-)-; GERANIOL

Drug Facts

Active ingredients

Avobenzone 3%
Homosalate 7%
Octisalate 4%
Octocrylene 7%

Purpose

Sunscreen

Uses

- helps prevent sunburn.
- if used as directed with other sun protection measures (see Directions), decreases the risk of skin cancer and early skin aging caused by the sun.

Warnings

For external use only.

Do not use

on damaged or broken skin.

When using this product

keep out of eyes. Rinse with water to remove.

Stop use and ask a doctor

if rash occurs.

Keep out of reach of children.

If swallowed, get medical help or contact a Poison Control Center right away.

Directions

For sunscreen use:

- apply generously 15 minutes before sun exposure.
- reapply at least every 2 hours
- use a water resistant sunscreen if swimming or sweating

- Sun Protection Measures. Spending time in the sun increases your risk of skin cancer and early

skin aging.To decrease this risk, regularly use a
sunscreen with a Broad Spectrum SPF value of
15 or higher and other sun protection measures
including:
• limit time in the sun, especially from 10 a.m.
- 2 p.m.
• wear long-sleeved shirts, pants, hats, and
sunglasses
• children under 6 months of age: Ask a doctor

Other information

- protect the product in this container from excessive heat and direct sun.
- You may report a serious adverse reaction to Report Reaction LLC, PO Box 22, Plainsboro, NJ 08536-0222.

Inactive ingredients

water, coco-caprylate/caprate, tribehenin
PEG-20 esters, glycerin, copernicia
cerifera (carnauba) wax, silica,
ethylhexylglycerin, caprylic/capric
triglyceride, phenoxyethanol, benzyl
alcohol, glycine soja (soybean) oil,
tocopherol, panthenol, lavandula
angustifolia (lavender) oil, acrylates/
C10-30 alkyl acrylate crosspolymer,
rosmarinus officinalis (rosemary)
leaf oil, sodium stearoyl glutamate,
trisodium ethylenediamine disuccinate,
microcrystalline cellulose, sodium
dehydroacetate, tocopheryl acetate,
cedrus atlantica (cedarwood) bark
oil, sodium hydroxide, cellulose gum,
sodium carrageenan, camellia sinensis
leaf extract, sea salt (maris sal), lactic
acid, sodium benzoate, beta-carotene,
daucus carota sativa (carrot) root extract,
potassium sorbate, linalool, limonene,
geraniol